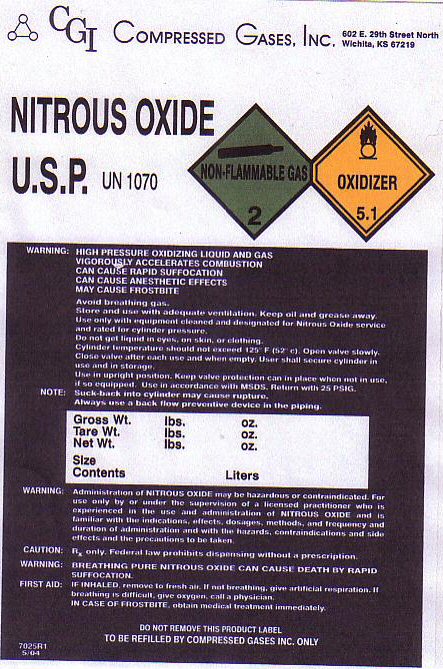 DRUG LABEL: NITROUS OXIDE
NDC: 34330-003 | Form: GAS
Manufacturer: Compressed Gases Inc
Category: prescription | Type: HUMAN PRESCRIPTION DRUG LABEL
Date: 20100101

ACTIVE INGREDIENTS: NITROUS OXIDE 99 L/100 L

NITROUS OXIDE USP LABEL

NITROUS OXIDE U.S.P. UN 1070 NON-FLAMMABLE-2 OXIDIZER-5.1

ADMINISTRATION OF NITROUS OXIDE MAY BE HAZARDOUS OR CONTRAINDICATED. FOR USE ONLY BY OR UNDER THE SUPERVISION OF A LICENSED PRACTITIONER WHO IS EXPERIENCED IN THE USE AND ADMINISTRATION OF NITROUS OXIDE AND IS FAMILIAR WITH THE INDICATIONS, EFFECTS, DOSAGES, METHODS, METHODS, AND FREQUENCY AND DURATION OF ADMINISTRATION AND WITH THE HAZARDS, CONTRAINDICATIONS AND SIDE EFFECTS AND THE PRECAUTIONS TO BE TAKEN.

CAUTION: Rx ONLY. FEDERAL LAW PROHIBITS DISPENSING WITHOUT A PRESCRIPTION.

GROSS WT________________ LBS____________ OZ

TARE WT ________________ LBS ______________ OZ

NET WT. _________________ LBS _______________ OZ

SIZE _______________ CONTENTS___________LITERS_____________

7025R1 5/04

PRODUCT WARNINGS AND PRECAUTIONS

WARNING: HIGH PRESSURE OXIDIZING LIQUID AND GAS. VIGOROUSLY ACCELERATES COMBUSTION. CAN CAUSE RAPID SUFFOCATION. CAN CAUSE ANESTHETIC EFFECTS. MAY CAUSE FROSTBITE. AVOID BREATHING GAS STORE AND USE WITH ADEQUATE VENTILATION. KEEP OIL AND GREASE AWAY. USE ONLY WITH EQUIPMENT CLEANED AND DESIGNATED FOR NITROUS OXIDE SERVICE AND RATED FOR CYLINDER PRESSURE. DO NOT GET LIQUID IN EYES ON SKIN OR CLOTHING. CYLINDER TEMPERATURE SHOULD NOT EXCEED 125 F (52 C) OPEN VALVE SLOWLY. CLOSE VALVE AFTER EACH USE AND WHEN EMPTY. USER SHALL SECURE CYLINDER IN USE AND IN STORAGE. USE IN UPRIGHT POSITION. KEEP VALVE PROTECTION CAP IN PLACE WHEN NOT IN USE IF SO EQUIPPED. USE IN ACCORDANCE WITH MSDS. RETURN WITH 25 PSIG.

NOTE: SUCK-BACK INTO CYLINDER MAY CAUSE RUPTURE. ALWAYS USE A BACK FLOW PREVENTATIVE DEVICE IN THE PIPING.

CAUTION: Rx ONLY. FEDERAL LAW PROHIBITS DISPENSING WITHOUT A PRESCRIPTION.

WARNING: BREATHING PURE NITROUS OXIDE CAN CAUSE DEATH BY RAPID SUFFOCATION.

FIRST AID: IF INHALED REMOVE TO FRESH AIR. IF NOT BREATHING GIVE ARTIFICIAL RESPIRATION. IF BREATHING IS DIFFICULT GIVE OXYGEN. CALL A PHYSICIAN. IN CASE OF FROSTBITE OBTAIN MEDICAL TREATMENT IMMEDIATELY.

DO NOT REMOVE THIS PRODUCT LABEL.